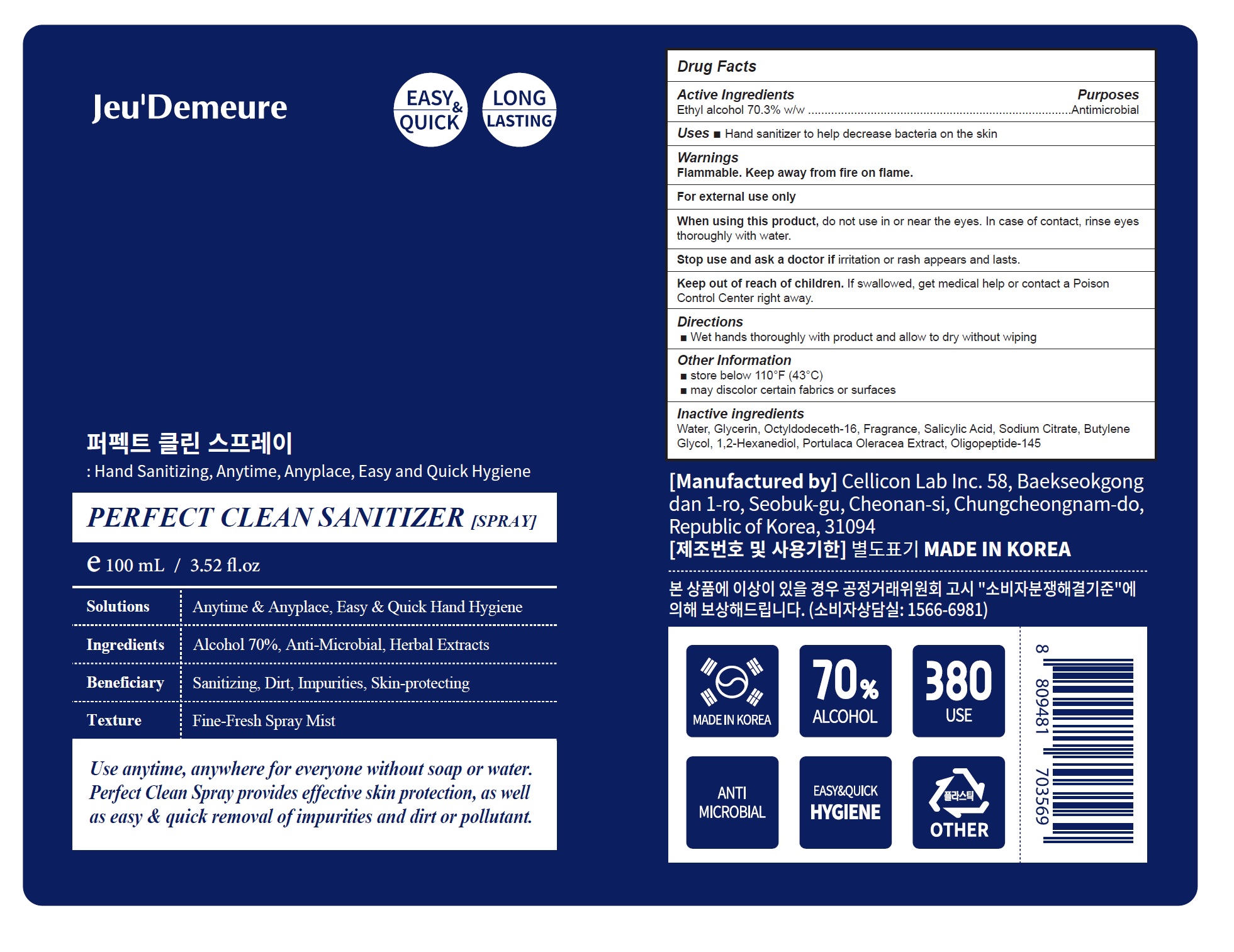 DRUG LABEL: PERFECT CLEAN SANITIZER
NDC: 81601-002 | Form: SPRAY
Manufacturer: Cellicon Lab Inc.
Category: otc | Type: HUMAN OTC DRUG LABEL
Date: 20210402

ACTIVE INGREDIENTS: ALCOHOL 0.703 mL/1 mL
INACTIVE INGREDIENTS: WATER; GLYCERIN; OCTYLDODECETH-16; SALICYLIC ACID; SODIUM CITRATE, UNSPECIFIED FORM; BUTYLENE GLYCOL; 1,2-HEXANEDIOL; PURSLANE

81601-002_PERFECT CLEAN SANITIZER

Active ingredient

Ethyl alcohol 70.3% w/w

Purpose

Antimicrobial

Use

- Hand sanitizer to help decrease bacteria on the skin

Warnings

Flammable. Keep away from fire or flame.

For external use only

When using this product do not use in or near the eyes. In case of contact, rinse eyes thoroughly with water.

Stop use and ask a doctor if irritation or rash appears and lasts

Keep out of reach of children.

Other information

- Store below 110°F (43°C)
- May discolor certain fabrics or surfaces

Directions

Wet hands thoroughly with product and allow to dry without wiping

Inactive ingredients

Water, Glycerin, Octyldodeceth-16, Fragrance, Salicylic Acid, Sodium Citrate, Butylene Glycol, 1,2-Hexanediol, Portulaca Oleracea Extract, Oligopeptide-145